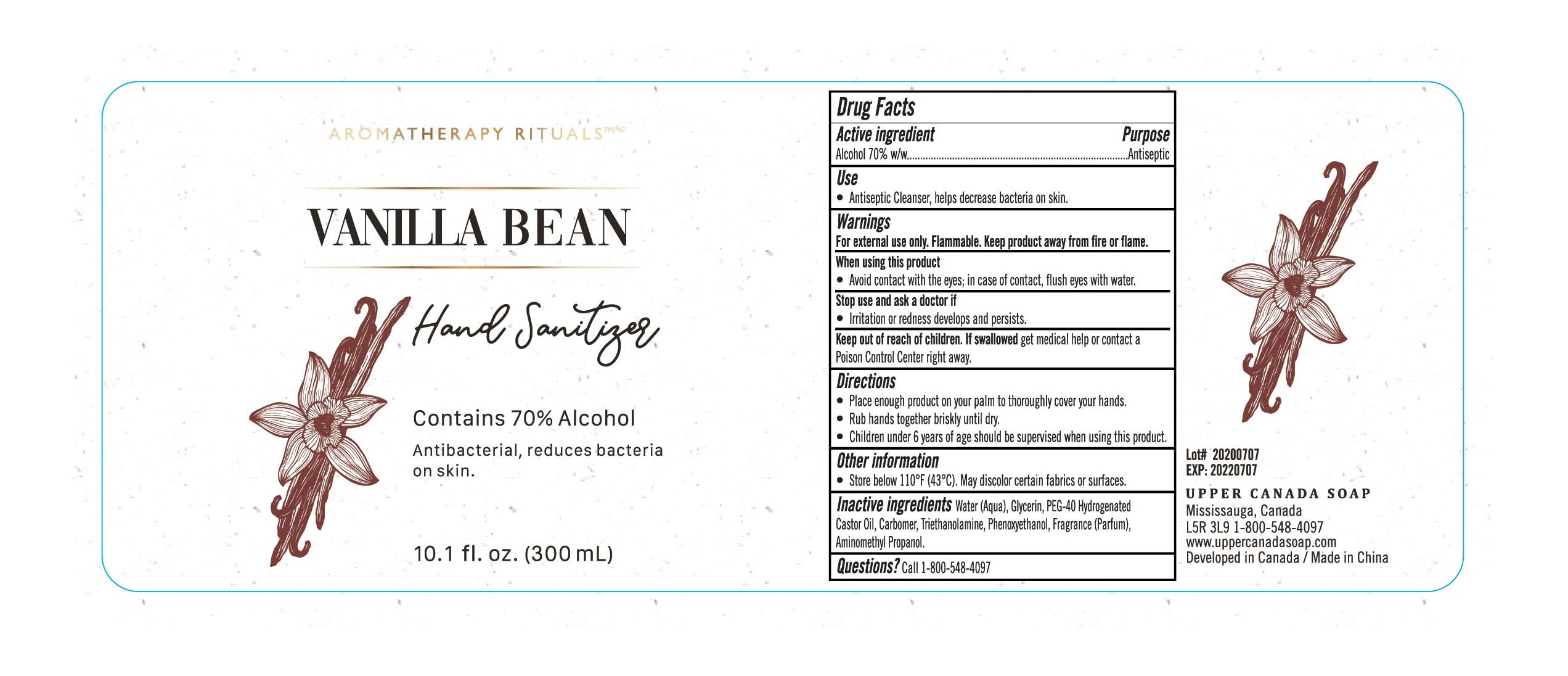 DRUG LABEL: Hand Sanitizer
NDC: 77607-002 | Form: GEL
Manufacturer: Xiamen Afgamarine Biotechnology Co., Ltd.
Category: otc | Type: HUMAN OTC DRUG LABEL
Date: 20201211

ACTIVE INGREDIENTS: ALCOHOL 210 mL/300 mL
INACTIVE INGREDIENTS: GLYCERIN; POLYOXYL 40 HYDROGENATED CASTOR OIL; WATER; TROLAMINE; PHENOXYETHANOL; FRAGRANCE LAVENDER & CHIA F-153480; AMINOMETHYLPROPANOL; CARBOMER HOMOPOLYMER, UNSPECIFIED TYPE

DOSAGE AND ADMINISTRATION

Store below 110°F (43"C). May discolor certain fabrics or surfaces.

INACTIVE INGREDIENT

WATER

GLYCERIN
PEG-40 Hydrogenated Castor Oil

CARBOMER

TRIETHANOLAMINE
Phenoxyethanol

Parfum (Fragrance)
Aminomethy propanol

INDICATIONS AND USAGE

●Place enough product on your palm to thoroughly cover your hands.
●Rub hands together biskly until dry.
●Children under 6 years of age should be supevised when using this product.

ACTIVE INGREDIENT

Alcohol

Keep out of reach of children. If swallowed get medial help or contact a Poison Control Center right away.

PURPOSE

Disinfection
Sterilization
No Rinseing

WARNINGS

For external use only, Flammable. Keep product away from fire or flame.